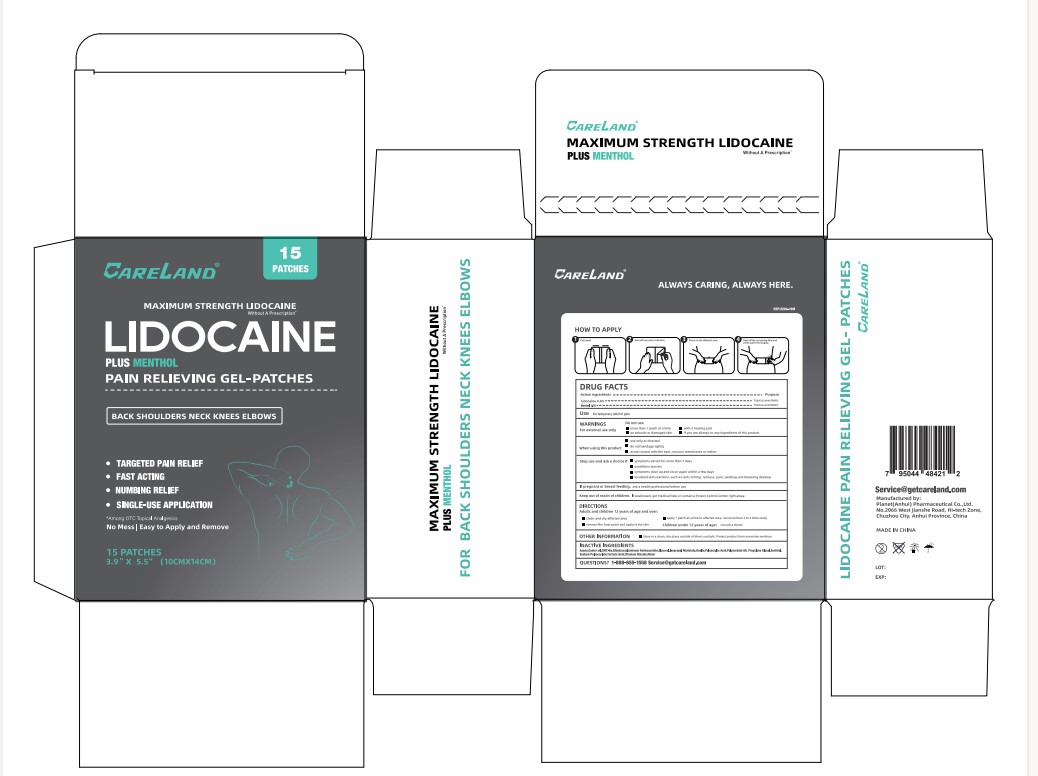 DRUG LABEL: Careland Lidocaine Plus Menthol Pain Relieving
NDC: 75568-016 | Form: PATCH
Manufacturer: Planet (Anhui) Pharmaceutical Co. Ltd.
Category: otc | Type: HUMAN OTC DRUG LABEL
Date: 20240424

ACTIVE INGREDIENTS: LIDOCAINE 80 mg/1 g; MENTHOL, UNSPECIFIED FORM 10 mg/1 g
INACTIVE INGREDIENTS: LAUROCAPRAM; CASTOR OIL; CMC-583; DIHYDROXYALUMINUM AMINOACETATE; GLYCERIN; ISOPROPYL MYRISTATE; KAOLIN; POLYACRYLIC ACID (250000 MW); POLYSORBATE 80; PROPYLENE GLYCOL MONOPALMITOSTEARATE; SORBITOL; SODIUM POLYACRYLATE (2500000 MW); TARTARIC ACID; TITANIUM DIOXIDE; WATER

Careland Lidocaine Plus Menthol Pain Relieving Gel-Patches

Drug Facts

Active Ingredients

Lidocaine 4.0%

Menthol 1.0%

Purpose

Topical Anesthetic

Use

for temperorary relief of pain

Warnings

For external use only

Do not use

- more than 1 patch at a time
- on wounds or damaged skin
- with a heating pad
- if you are allergic to any ingredients of this product

when using this product

- use only as directed
- do not bandage tightly
- avoid contact with the eyes, mucous membranes or rashes

Stop use and ask a doctor if

- symptoms persist for more than 7 days
- conditions worsen
- symptoms clear up and occur again within few days
- localized skin reactions, such as rash, itching, redness, pain, swelling and blistering develop

If pregnant or breasatfeeding,

ask a health professional before use

Keep out of reach of children.

If swallowed, get medical help or contact a Poison Control Center right away.

Directions

Adults and Children 12 years of age and over:

- clean and dry affected area
- remove film from patch and apply to skin
- apply 1 patch at a time to affected area, not more than 3 to 4 times daily
- CHildren under 12 years of age: cnsult a doctor

Other Information

Store in a clean, dry place outside of direct sunlight. Protect product from excessive moisture

Inactive Ingredients

Azone, Castor oil, CMC-Na, Dihydroxyaluminum Aminoacetate, Glycerol, Isopropyl Myristate, Kaolin, Polyacrylic Acid, Polysorbate 80, Propylene Glycol, Sorbitol, Sodium Polyacrylate, Tartaric Acid, Titanium Dioxide, Water

Questions?

1-888-655-1558 Service@getcareland.com